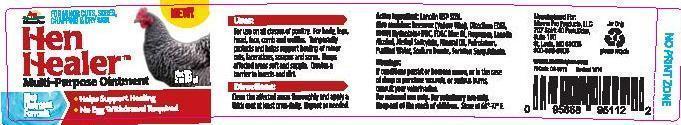 DRUG LABEL: HEN HEALER  MULTI-PURPOSE
NDC: 86077-0033 | Form: OINTMENT
Manufacturer: Manna Pro Products LLC
Category: animal | Type: OTC ANIMAL DRUG LABEL
Date: 20241213

ACTIVE INGREDIENTS: LANOLIN 30 g/100 g

Hen Healer Multi-Purpose Ointment

Drug Facts

Active Ingredient: Lanolin 30%

Purpose: Skin protectant

Purpose - Skin protectant

Uses:

For use on all classes of poultry. For body, legs, head, face, comb and wattles. Temporarily protects and helps support healing of minor cuts, lacerations, scrapes and sores. Keeps affected areas soft and supple. Creates a barrier to insects and dirt.

Warnings:

If conditions persist or become worse, or in the case of deep or puncture wounds, or serious burns, consult your veterinarian.

Keep out of the reach of children.

Directions:

Clean the affected area thoroughly and apply a thick coat at least once daily. Repeat as needed.

Other Information

Store at 68-77 degrees F.

Inactive Ingredients

Beeswax (yellow wax), Disodium EDTA, DMDM Hydantoin+IPBC, FD&C Blue #1, Fragrance, Lanolin Alcohol, Methyl Salicylate, Mineral Oil, Petrolatum, Purified Water, Sodium Borate, Sorbitan Sesquioleate.

For questions or comments

call 1-800-690-9908 or visit www.mannapro.com

PACKAGE LABEL

For Minor Cuts, Sores, Chapping & Dry Skin

NEW

HEN HEALER MULTI-PURPOSE OINTMENT

Blue Ointment Formula

Helps Support Healing

No Egg Withdrawal Required

Manna Pro Products, LLC

707 Spirit 40 Park Dr.

Suite 150

St. Louis, MO 63005